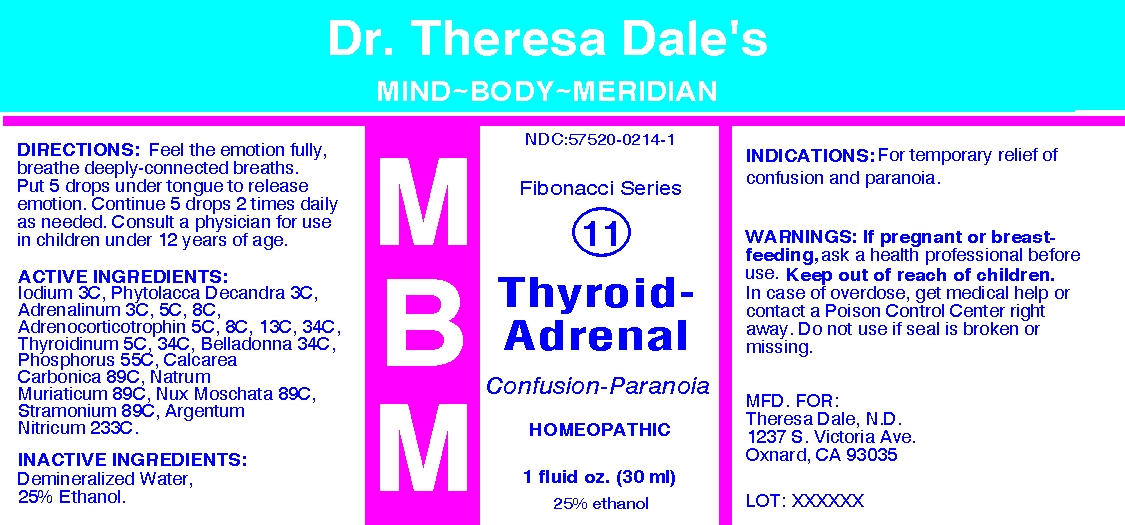 DRUG LABEL: MBM 11 Thyroid Adrenal
NDC: 57520-0214 | Form: LIQUID
Manufacturer: Apotheca Company
Category: homeopathic | Type: HUMAN OTC DRUG LABEL
Date: 20100629

ACTIVE INGREDIENTS: IODINE 3 [hp_C]/1 mL; PHYTOLACCA AMERICANA ROOT 3 [hp_C]/1 mL; EPINEPHRINE 8 [hp_C]/1 mL; CORTICOTROPIN 34 [hp_C]/1 mL; THYROID 34 [hp_C]/1 mL; ATROPA BELLADONNA 34 [hp_C]/1 mL; PHOSPHORUS 55 [hp_C]/1 mL; OYSTER SHELL CALCIUM CARBONATE, CRUDE 89 [hp_C]/1 mL; SODIUM CHLORIDE 89 [hp_C]/1 mL; NUTMEG 89 [hp_C]/1 mL; DATURA STRAMONIUM 89 [hp_C]/1 mL; SILVER NITRATE 233 [hp_C]/1 mL
INACTIVE INGREDIENTS: WATER; ALCOHOL

MBM 11 Thyroid Adrenal

ACTIVE INGREDIENT

ACTIVE INGREDIENTS: Iodium 3C, Phytolacca decandra 3C, Adrenalinum 3C, 5C, 8C, Adrenocotricotrophin 5C, 8C, 13C, 34C, Thyroidinum 5C, 34C, Belladona 34C, Phosphorus 55C, Calcarea Carbonica 89C, Natrum muriaticum 89C, Nux moschata 89C, Stramonium 89C, Argentum nitricum 233C.

PURPOSE

INDICATIONS: For temporary relief of confusion and paranoia.

WARNINGS

WARNINGS: If pregnant or breast-feeding, ask a health professional before use. Keep out of reach of children. In case of overdose, get medical help or contact a Poison Control Center right away. Do not use if seal is broken or missing.

DOSAGE AND ADMINISTRATION

DIRECTIONS: Feel the emotion fully, breathe deeply-connected breaths. Put 5 drops under tongue to release emotion. Continue 5 drops 2 times daily as needed. Consult a physician for use in children under 12 years of age.

INACTIVE INGREDIENTS: Demineralized water, 25% Ethanol

QUESTIONS

MFD. FOR:

Theresa Dale, N. D.

1237 S. Victoria Ave.

Oxnard, CA 93035

PACKAGE LABEL

Dr. Theresa Dale's

Mind-Body-Meridian

Fibonacci Series

11

THYROID-ADREANAL

Confusion-Paranoia

HOMEOPATHIC

1 FLUID OZ. (30 ML)